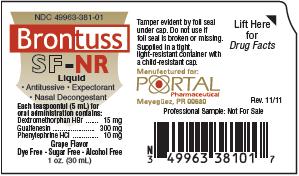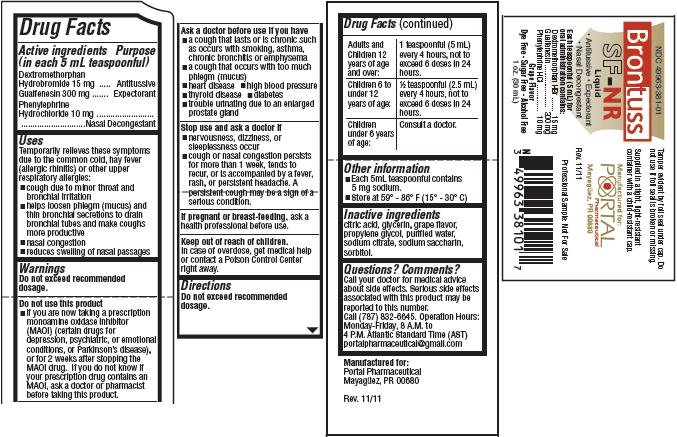 DRUG LABEL: Brontuss
NDC: 49963-381 | Form: LIQUID
Manufacturer: Portal Pharmaceutical
Category: otc | Type: HUMAN OTC DRUG LABEL
Date: 20111214

ACTIVE INGREDIENTS: Dextromethorphan Hydrobromide 15 mg/5 mL; Guaifenesin 300 mg/5 mL; Phenylephrine Hydrochloride 10 mg/5 mL
INACTIVE INGREDIENTS: Citric Acid Monohydrate; Glycerin; Water; Sodium Citrate; Saccharin Sodium; Sorbitol

Brontuss SF-NR

Drug Facts

Active ingredients
(in each 5 mL teaspoonful)
Dextromethorphan Hydrobromide 15 mg
Guaifenesin 300 mg
Phenylephrine Hydrochloride 10 mg

Purpose

Antitussive
Expectorant
Nasal Decongestant

Uses

Temporarily relieves these symptoms due to the common cold, hay fever (allergic rhinitis) or other upper respiratory allergies:

- cough due to minor throat and bronchial irritation
- helps phlegm (mucus) and thin bronchial secretions to drain bronchial tubes and make coughs more productive
- nasal congestion
- reduces swelling of nasal passages

Warnings

Do not exceed recommended dosage.

Do not use this product

- if you are now taking a prescription monoamine oxidase inhibitor (MAOI) (certain drugs for depression, psychiatric, or emotional conditions, or Parkinson's disease), or for 2 weeks after stopping the MAOI drug. If you do not know if your prescription drug contains an MAOI, ask a doctor or pharmacist before taking this product.

Ask a doctor before use if you have

- a cough that lasts or is chronic such as occurs with smoking, asthma, chronic bronchitis or emphysema
- a cough that occurs with too much phlegm (mucus)
- heart disease
- high blood pressure
- thyroid disease
- diabetes
- trouble urinating due to an enlarged prostate gland

Stop use and ask a doctor if

- nervousness, dizziness, or sleeplessness occur
- cough or nasal congestion persists for more than 1 week, tends to recur, or is accompanied by a fever, rash, or persistent headache. A persistent cough may be a sign of a serious condition.

PREGNANCY OR BREAST FEEDING

If pregnant or breast-feeding, ask a health professional before use.

Keep out of reach of children.

In case of overdose, get medical help or contact a Poison Control Center right away.

Directions

Do not exceed recommended dosage.

Adults and Children 12 years of age and over: | 1 teaspoonful (5 mL) every 4 hours, not to exceed 6 doses in 24 hours.
Children 6 to under 12 years of age: | 1/2 teaspoonful (2.5 mL) every 4 hours, not to exceed 6 doses in 24 hours.
Children under 6 years of age: | Consult a doctor.

Other information

- Each 5 mL teaspoonful contains 5 mg sodium.
- Store at 59°-86° F (15°-30° C)

Inactive ingredients

citric acid, glycerin, grape flavor, propylene glycol, purified water, sodium citrate, sodium saccharin, sorbitol.

Questions? Comments?

Call your doctor for medical advice about side effects. Serious side effects associated with this product may be reported to this number.
Call (787) 832-6645. Operation Hours: Monday - Friday, 8 A.M. to 4 P.M. Atlantic Standard Time (AST)
portalpharmaceutical@gmail.com
Manufactured for:
Portal Pharmaceutical
Mayaguez, PR 00681
Rev. 11/11

Product Packaging

The packaging below represents the labeling currently used.
Principal display panel and side panel for 30 mL label:
NDC 49963-381-01
Brontuss
SF-NR
Liquid
· Antitussive · Expectorant
· Nasal Decongestant
Each teaspoonful (5 mL) for
oral administration contains:
Dextromethorphan HBr....................15 mg
Guaifenesin..................................300 mg
Phenylephrine HCl..........................10 mg
Grape Flavor
Dye Free · Sugar Free · Alcohol Free
1 oz. (30 mL)
Tamper evident by foil seal under cap. Do not use if
foil seal is broken or missing.
Supplied in a tight, light-resistant container with a child-
resistant cap.
Manufactured for:
PORTAL
Pharmaceutical
Mayaguez, PR 00680 Rev. 11/11
Professional Sample: Not For Sale